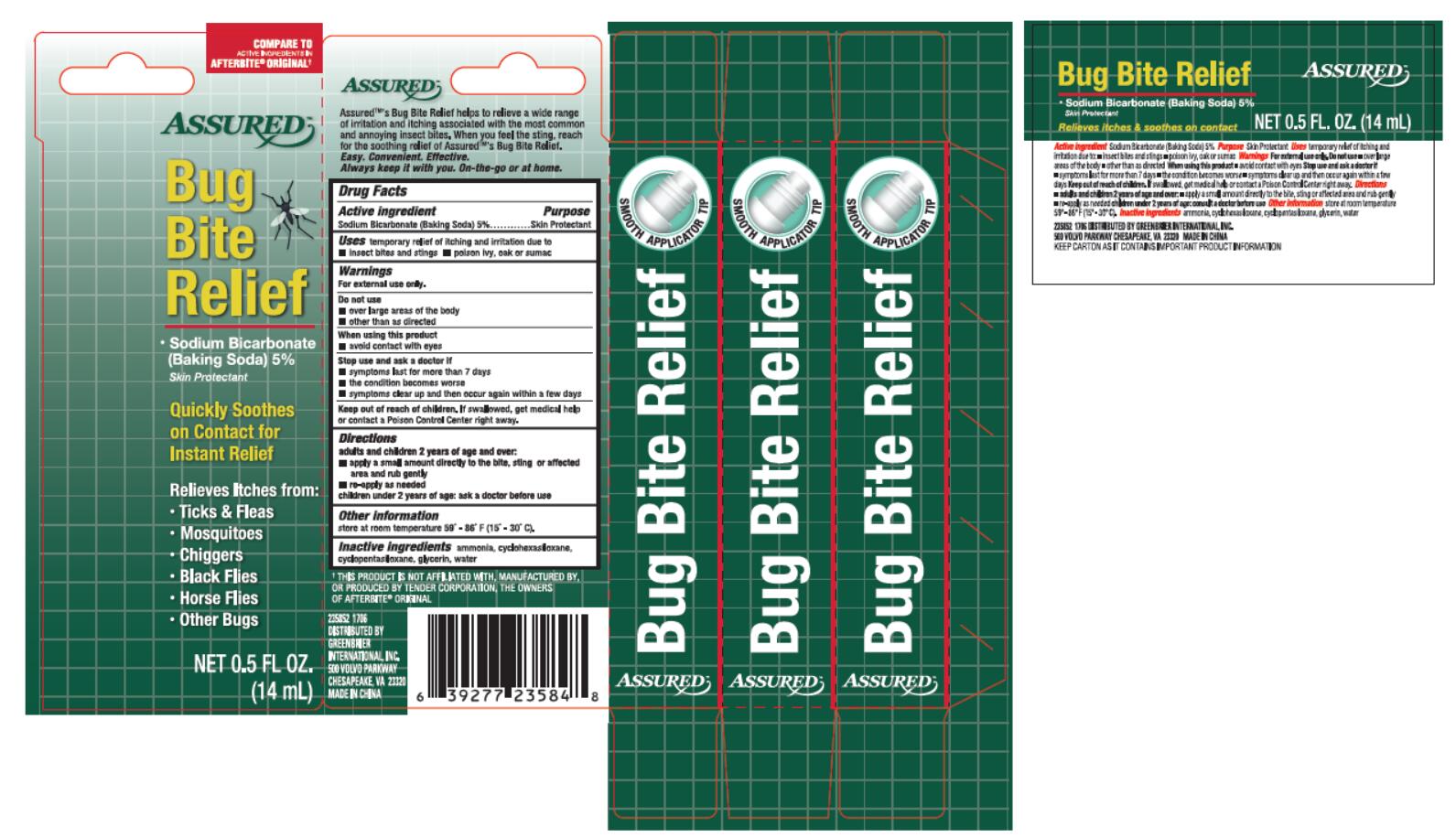 DRUG LABEL: Assured
NDC: 71537-005 | Form: LIQUID
Manufacturer: Huijing (Shanghai) Bio-tech Co., Ltd
Category: otc | Type: HUMAN OTC DRUG LABEL
Date: 20171212

ACTIVE INGREDIENTS: SODIUM BICARBONATE 5 g/100 mL
INACTIVE INGREDIENTS: AMMONIA; CYCLOMETHICONE 6; CYCLOMETHICONE 5; GLYCERIN; WATER

Active ingredient

Sodium Bicarbonate(Baking Soda) 5%

Purpose

Skin Protectant

INDICATIONS AND USAGE

Uses temporary relief of itching and irritation due to

•insect bites and stings •poison ivy, oak or sumac

Warnings

For external use only.

Do not use

•over large areas of the body

•other than as directed

When using this product

•avoid contact with eyes

Stop use and ask a doctor if

•symptoms last for more than 7 days

•the condition becomes worse

•symptoms clear up and then occur again within a few days

Keep out of reach of children. If swallowed, get medical help

or contact a Poison control Center right away.

Directions

adults and children 2 years of age and over:

•apply a small amount directly to the bite, sting or affected

area and rub gently

•re-apply as needed

children under 2 years of age: ask a doctor before use

Other information

store at room temperature 59° - 86° F (15° - 30°C).

Inactive ingredients ammonia, cyclohexasiloxane,

cyclopentasiloxane, glycerin, water